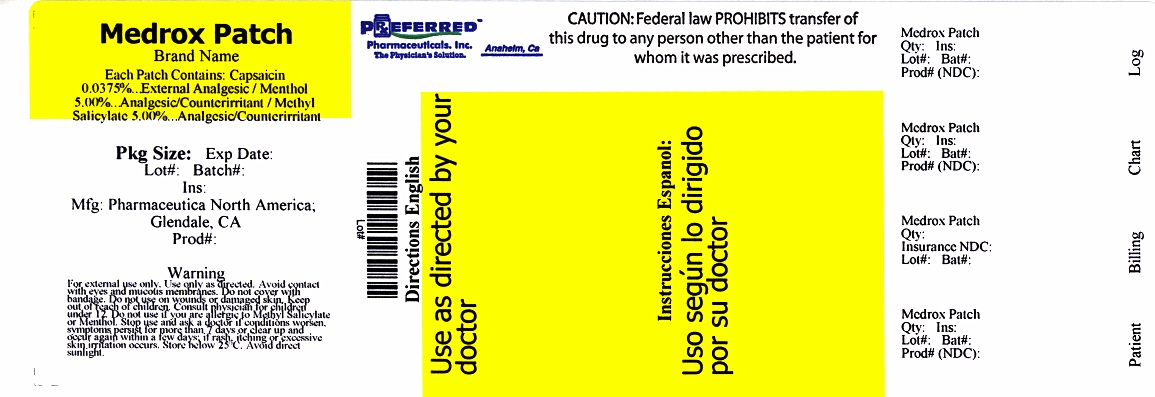 DRUG LABEL: MEDROX
NDC: 68788-6755 | Form: PATCH
Manufacturer: Preferred Pharmaceuticals, Inc.
Category: otc | Type: HUMAN OTC DRUG LABEL
Date: 20171220

ACTIVE INGREDIENTS: MENTHOL, UNSPECIFIED FORM 5 g/100 g; CAPSAICIN 0.0375 g/100 g
INACTIVE INGREDIENTS: WATER; GLYCERIN; POLYSORBATE 80; ALOE VERA LEAF; EDETATE DISODIUM; DIAZOLIDINYL UREA; METHYLPARABEN; IODOPROPYNYL BUTYLCARBAMATE; PROPYLPARABEN

MEDROX PATCH

ACTIVE INGREDIENTS

Menthol 5.00%

Capsaicin 0.0375%

PURPOSE

Analgesic/Counterirritant

External Analgesic

USES

Use for the temporary relief of minor aches and muscle pains associated with arthritis, simple backache, strains, muscle soreness and stiffness.

WARNINGS

- •For external use only. Use only as directed. Avoid contact with eyes and mucous membranes.
- •Do not cover with bandage.
- •Do not use on wounds or damaged skin.
- •Consult physician for children under 12.
- •Do not use if you are allergic to Menthol
- •Stop use and ask a doctor if conditions worsen, symptoms persist for more than 7 days or clear up and occur again within a few days
- •Or rash, itching or excessive skin irritation occurs.

DIRECTIONS

- •Adults and children 12 years and over apply to affected area: change patch 1 to 2 times daily
- •Children under 12 years, consult physician before use
- •How to apply:
- •Clean and dry affected area
- •Cut open pouch and remove patch
- •Remove protective film and apply directly to area of pain
- •Apply to affected area not more than 3 times daily
- •Wash hands with soap after applying patch
- •Reseal pouch containing unused patches

OTHER INGREDIENTS

Water, Glycerine, Sodium Polyacrylate, Polysorbate 80, Aloe Barbadensis Leaf (Aloe Vera Gel) Juice, EDTA Disodiumm Salt, Diazolidinyl Urea, Methylparaben, Iodoproynyl Butylcabamate, Propylparaben.

HOW SUPPLIED

5 Patches – 68788-6755-5

30 Patches – 68788-6755-3

Relabeled by Preferred Pharmaceuticals, Inc.